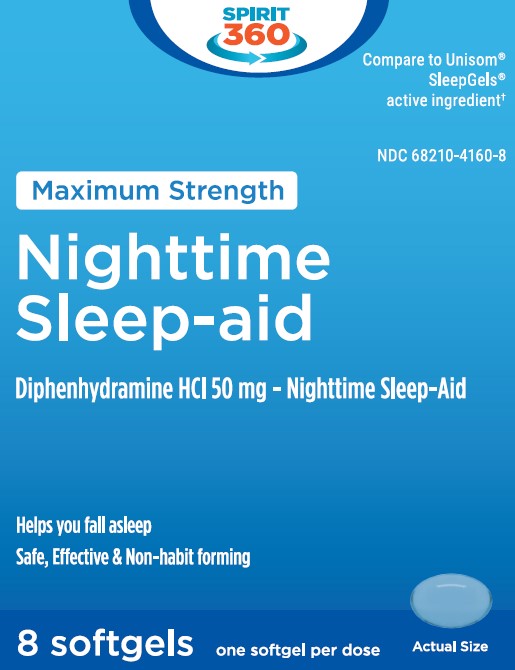 DRUG LABEL: NIGHTTIME SLEEP AID
NDC: 68210-4160 | Form: CAPSULE, LIQUID FILLED
Manufacturer: Prodose, Inc.
Category: otc | Type: HUMAN OTC DRUG LABEL
Date: 20260126

ACTIVE INGREDIENTS: DIPHENHYDRAMINE HYDROCHLORIDE 50 mg/1 1
INACTIVE INGREDIENTS: FD&C BLUE NO. 1; GELATIN; GLYCERIN; POLYETHYLENE GLYCOL 400; PROPYLENE GLYCOL; SORBITOL; TITANIUM DIOXIDE; WATER

NIGHTTIME SLEEP-AID

Drug Facts

Active ingredient (in each softgel)

Diphenhydramine HCL 50 mg

Purpose

Nighttime sleep-aid

Uses

- for relief of occasional sleeplessness
- reduces time to fall asleep if you have difficulty falling asleep

Warnings

Do not use

- for children under 12 years of age
- with any other product containing diphenhydramine, even one used on skin

Ask a doctor before use if you have

- a breathing problem such as emphysema or chronic bronchitis
- glaucoma
- trouble urinating due to an enlarged prostate gland

Ask a doctor or pharmacist before use if you are taking sedatives or tranquilizers

When using this product

avoid alcoholic drinks

Stop use and ask a doctor if

sleeplessness persist continuously for more than 2 weeks. Insomnia may be a symptom of serious underlying medical illness.

PREGNANCY OR BREAST FEEDING

If pregnant or breast-feeding, ask a health professional before use.

Keep out of reach of children.

In case of overdose, get medical help or contact a Poison Control Center right away. 1(800)222-1222

Directions

- adults and children 12 years of age and over: 1 softgel (50 mg) at bedtime if needed, or as directed by a doctor

Inactive ingredients

FD&C Blue#1, gelatin, glycerin, polyethylene glycol-400, propylene glycol, sorbitol, titanium dioxide, water

Questions or comments?

1-888-333-9792

PRINCIPAL DISPLAY PANEL

NDC 68210-4160-8

Maximum Strength

Nighttime Sleep-aid

Diphenhydramine HCl 50 mg - Nighttime Sleep-Aid

Helps you fall asleep
Safe, Effective & Non-habit forming

8 softgels

one softgel per dose